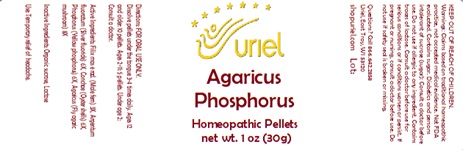 DRUG LABEL: Agaricus Phosphorus
NDC: 48951-1023 | Form: PELLET
Manufacturer: Uriel Pharmacy Inc.
Category: homeopathic | Type: HUMAN OTC DRUG LABEL
Date: 20241022

ACTIVE INGREDIENTS: DRYOPTERIS FILIX-MAS ROOT 3 [hp_X]/1 1; SILVER FLUORIDE 6 [hp_X]/1 1; OSTREA EDULIS SHELL 6 [hp_X]/1 1; PHOSPHORUS 6 [hp_X]/1 1; AMANITA MUSCARIA FRUITING BODY 8 [hp_X]/1 1
INACTIVE INGREDIENTS: SUCROSE; LACTOSE

Agaricus Phosphorus

INDICATIONS AND USAGE

Directions: FOR ORAL USE ONLY.

DOSAGE AND ADMINISTRATION

Dissolve pellets under the tongue 3-4 times daily. Ages 12 and older: 10 pellets. Ages 2-11: 5 pellets. Under age 2: Consult a doctor.

ACTIVE INGREDIENT

Active Ingredients: Filix mas e rad (Male fern) 3X, Argentum fluoratum (Silver fluoride) 6X, Conchae (Oyster shells) 6X, Phosphorus (Yellow phosphorus) 6X, Agaricus (Fly agaric mushroom) 8X

Inactive Ingredients: Organic sucrose, Lactose

Prepared using rhythmical processes

PURPOSE

Use: Temporary relief of headache.

KEEP OUT OF REACH OF CHILDREN.

WARNINGS

Warnings: Claims based on traditional homeopathic practice, not accepted medical evidence. Not FDA evaluated. Contains sugar. Diabetics and persons intolerant of sucrose (sugar): Consult a doctor before use. Do not use if allergic to any ingredient. Contains traces of lactose. Consult a doctor before use for serious conditions or if conditions worsen or persist. If pregnant or nursing, consult a doctor before use. Do not use if safety seal is broken or missing.

QUESTIONS

Questions? Call 866.642.2858 Uriel, East Troy WI 53120 shopuriel.com Lot: